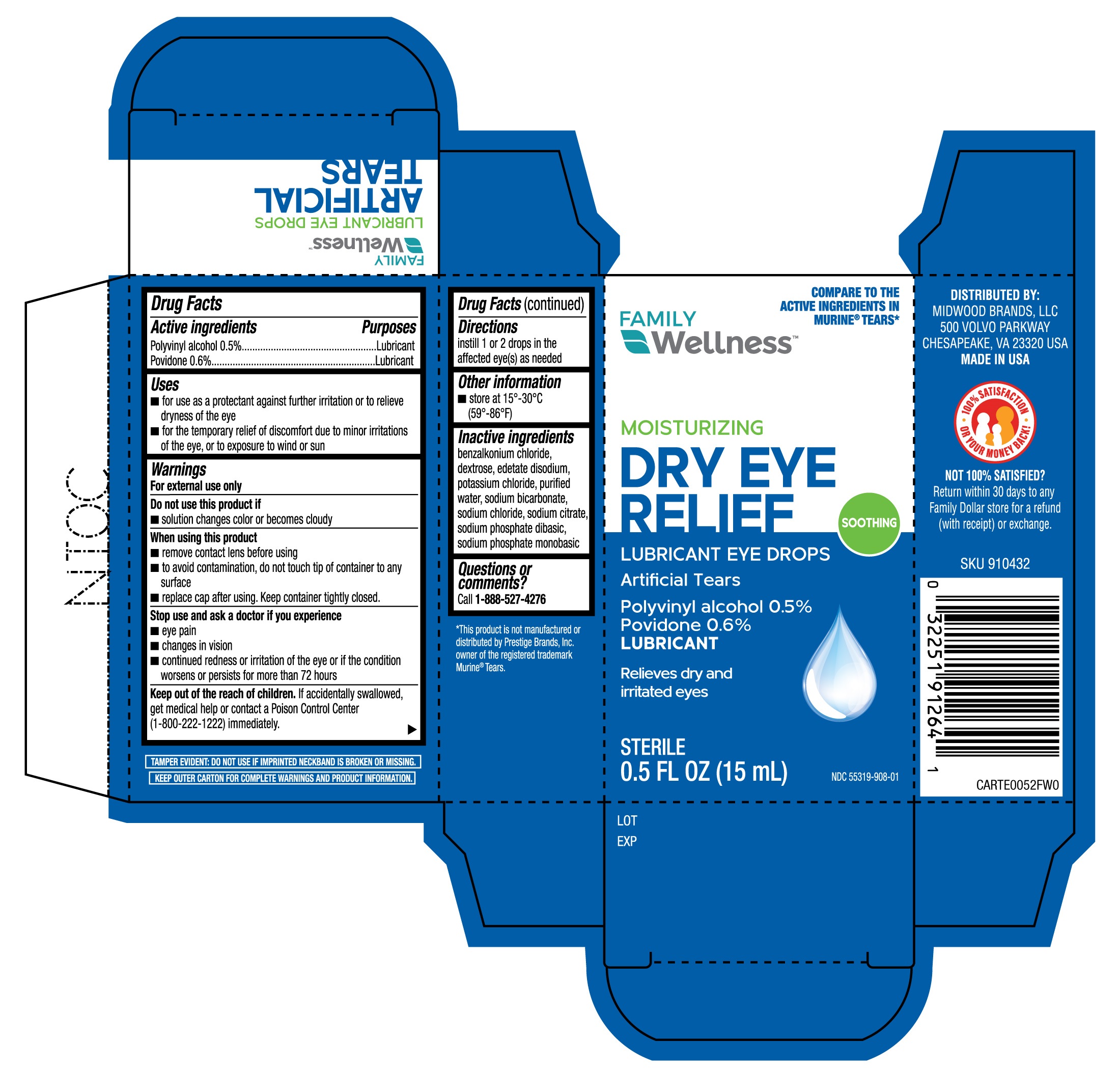 DRUG LABEL: Family Wellness Artificial Tears
NDC: 55319-908 | Form: SOLUTION/ DROPS
Manufacturer: Family Dollar Services, Inc.
Category: otc | Type: HUMAN OTC DRUG LABEL
Date: 20251230

ACTIVE INGREDIENTS: POVIDONE 0.6 g/100 mL; POLYVINYL ALCOHOL, UNSPECIFIED 0.5 g/100 mL
INACTIVE INGREDIENTS: SODIUM CHLORIDE; SODIUM PHOSPHATE, DIBASIC; SODIUM BICARBONATE; SODIUM PHOSPHATE, MONOBASIC; POTASSIUM CHLORIDE; BENZALKONIUM CHLORIDE; DEXTROSE; SODIUM CITRATE; EDETATE DISODIUM; WATER

Family Wellness Artificial Tears 15mL (PLD)

Active ingredients

Polyvinyl alcohol 0.5%

Povidone 0.6%

Purposes

Lubricant

Lubricant

Uses

- for use as a protectant against further irritation or to relieve dryness of the eye
- for the temporary relief of discomfort due to minor irritations of the eye, or to exposure to wind or sun

Warnings

For external use only

Do not use this product if

- solution changes color or becomes cloudy

When using this product

- remove contact lens before using
- to avoid contamination, do not touch tip of container to any surface
- replace cap after using. Keep container tightly closed.

Stop use and ask a doctor if

you experience

- eye pain
- changes in vision
- continued redness or irritation of the eye or if the condition worsens or persists for more than 72 hours

Keep out of the reach of children.

If accidentally swallowed, get medical help or contact a Poison Control Center (1-800-222-1222) immediately.

Directions

instill 1 or 2 drops in the affected eye(s) as needed

Other information

- store at 15°-30°C (59°-86°F)

Inactive ingredients

benzalkonium chloride, dextrose, edetate disodium, potassium chloride, purified water, sodium bicarbonate, sodium chloride, sodium citrate, sodium phosphate dibasic, sodium phosphate monobasic

Questions or comments?

Call 1-888-527-4276